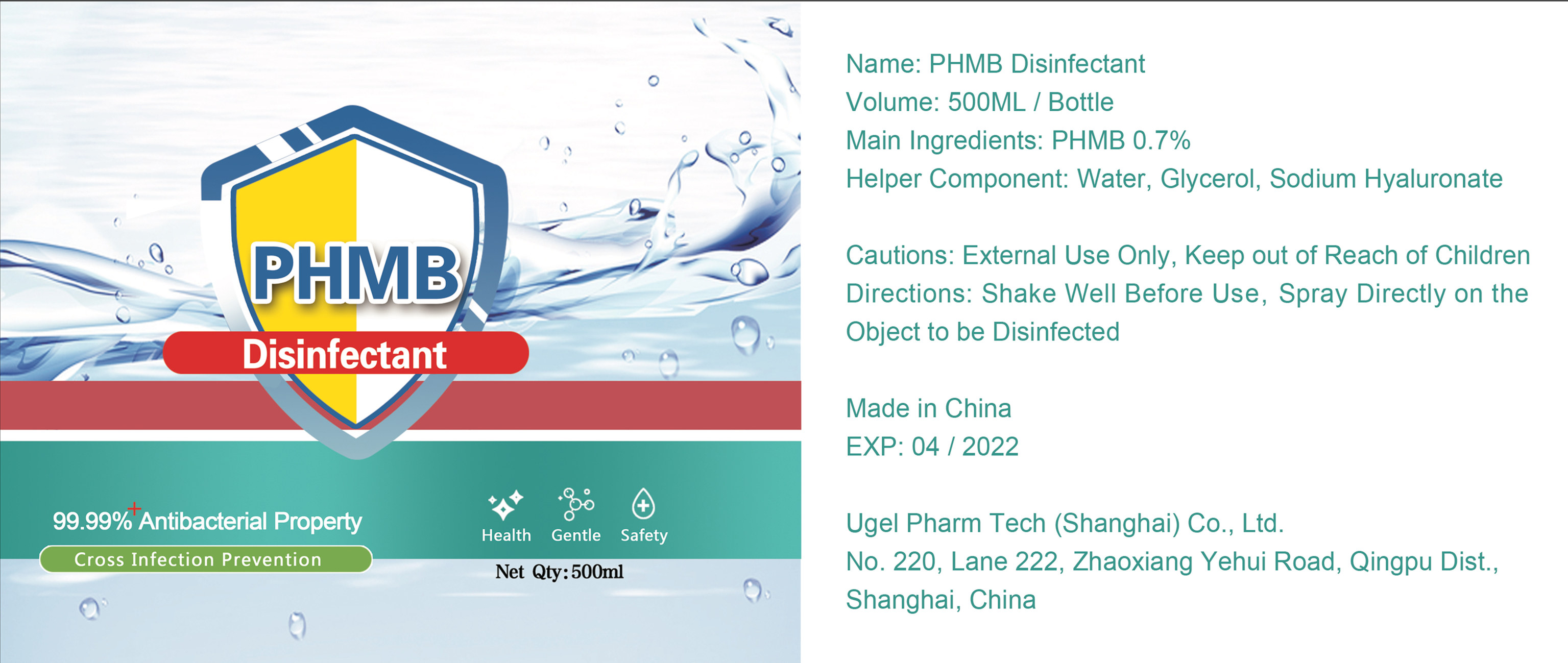 DRUG LABEL: PHMB Disinfectant
NDC: 55262-001 | Form: SPRAY
Manufacturer: Ugel Pharm Tech (Shanghai) Co., Ltd.
Category: otc | Type: HUMAN OTC DRUG LABEL
Date: 20200522

ACTIVE INGREDIENTS: POLIHEXANIDE HYDROCHLORIDE 3.5 g/500 mL
INACTIVE INGREDIENTS: HYALURONATE SODIUM; ALCOHOL; WATER

DOSAGE AND ADMINISTRATION

Store in a cool and dry place

INACTIVE INGREDIENT

Water, Glycerol, Sodium Hyaluronate

INDICATIONS AND USAGE

Shake Well Before Use, Spray Directly on the Object to be Disinfected

ACTIVE INGREDIENT

PHMB

keep out of reach of children

PURPOSE

Disinfection
Sterilization

WARNINGS

External Use Only, Keep out of Reach of Children